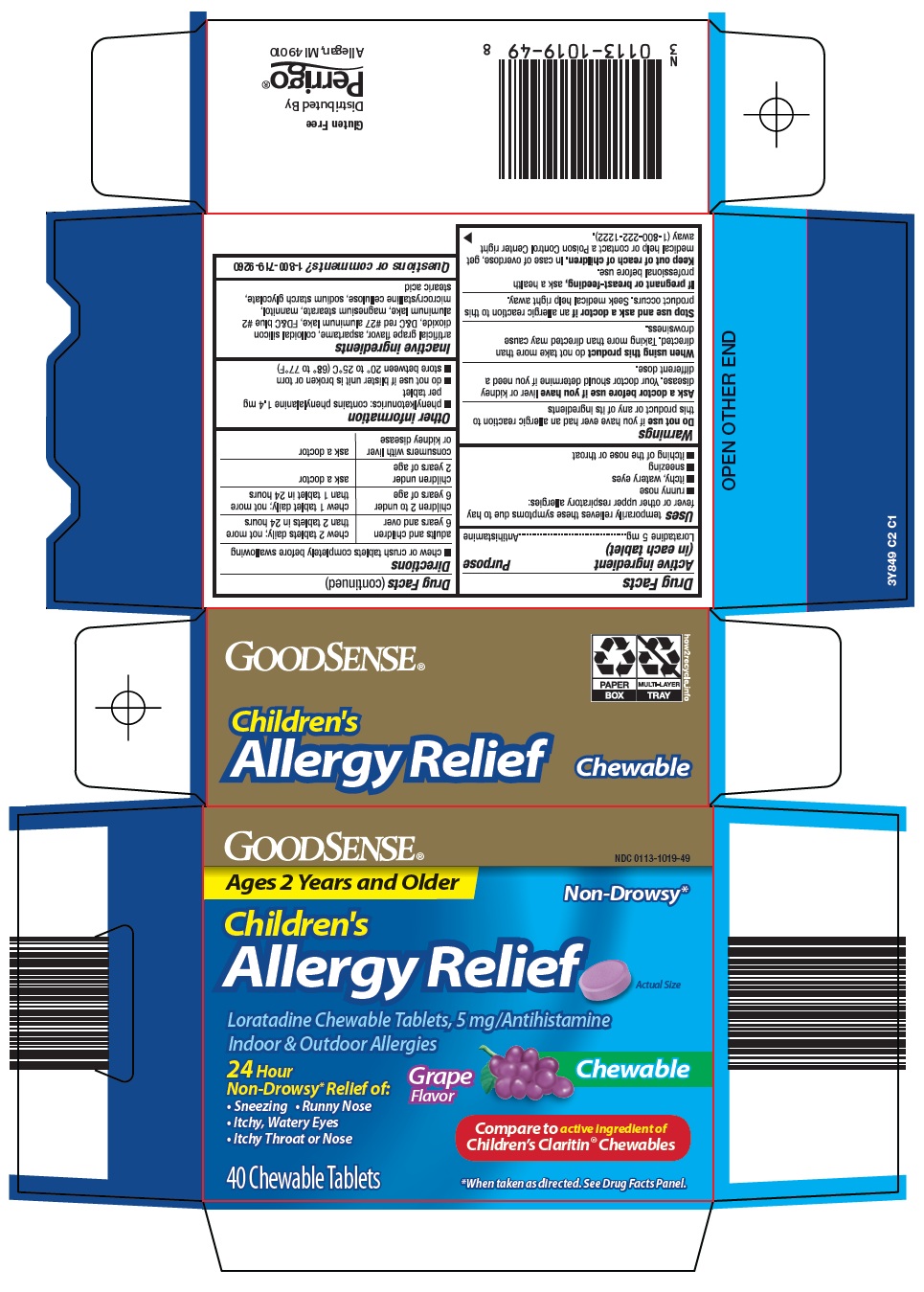 DRUG LABEL: good sense childrens allergy relief
NDC: 0113-1019 | Form: TABLET, CHEWABLE
Manufacturer: L. Perrigo Company
Category: otc | Type: HUMAN OTC DRUG LABEL
Date: 20251114

ACTIVE INGREDIENTS: LORATADINE 5 mg/1 1
INACTIVE INGREDIENTS: ASPARTAME; SILICON DIOXIDE; D&C RED NO. 27; FD&C BLUE NO. 2; MAGNESIUM STEARATE; MANNITOL; MICROCRYSTALLINE CELLULOSE; STEARIC ACID

Perrigo Children’s Allergy Relief Drug Facts

Active ingredient (in each tablet)

Loratadine 5 mg

Purpose

Antihistamine

Uses

temporarily relieves these symptoms due to hay fever or other upper respiratory allergies:

- runny nose
- itchy, watery eyes
- sneezing
- itching of the nose or throat

Warnings

Do not use

if you have ever had an allergic reaction to this product or any of its ingredients

Ask a doctor before use if you have

liver or kidney disease. Your doctor should determine if you need a different dose.

When using this product

do not take more than directed. Taking more than directed may cause drowsiness.

Stop use and ask a doctor if

an allergic reaction to this product occurs. Seek medical help right away.

If pregnant or breast-feeding,

ask a health professional before use.

Keep out of reach of children.

In case of overdose, get medical help or contact a Poison Control Center right away (1-800-222-1222).

Directions

- chew or crush tablets completely before swallowing

adults and children 6 years and over | chew 2 tablets daily; not more than 2 tablets in 24 hours
children 2 to under 6 years of age | chew 1 tablet daily; not more than 1 tablet in 24 hours
children under 2 years of age | ask a doctor
consumers with liver or kidney disease | ask a doctor

Other information

- phenylketonurics: contains phenylalanine 1.4 mg per tablet
- do not use if blister unit is broken or torn
- store between 20° to 25°C (68° to 77°F)

Inactive ingredients

artificial grape flavor, aspartame, colloidal silicon dioxide, D&C red #27 aluminum lake, FD&C blue #2 aluminum lake, magnesium stearate, mannitol, microcrystalline cellulose, sodium starch glycolate, stearic acid

Questions or comments?

1-800-719-9260

Principal Display Panel

GOODSENSE®

Ages 2 Years and Older

Non-Drowsy*

Children’s Allergy Relief

Actual Size

Loratadine Chewable Tablets, 5 mg/Antihistamine

Indoor & Outdoor Allergies

24 Hour Non-Drowsy* Relief of:

• Sneezing

• Runny Nose

• Itchy, Watery Eyes

• Itchy Throat or Nose

Grape Flavor

Chewable

Compare to active ingredient of Children’s Claritin® Chewables

40 Chewable Tablets

*When taken as directed. See Drug Facts Panel.